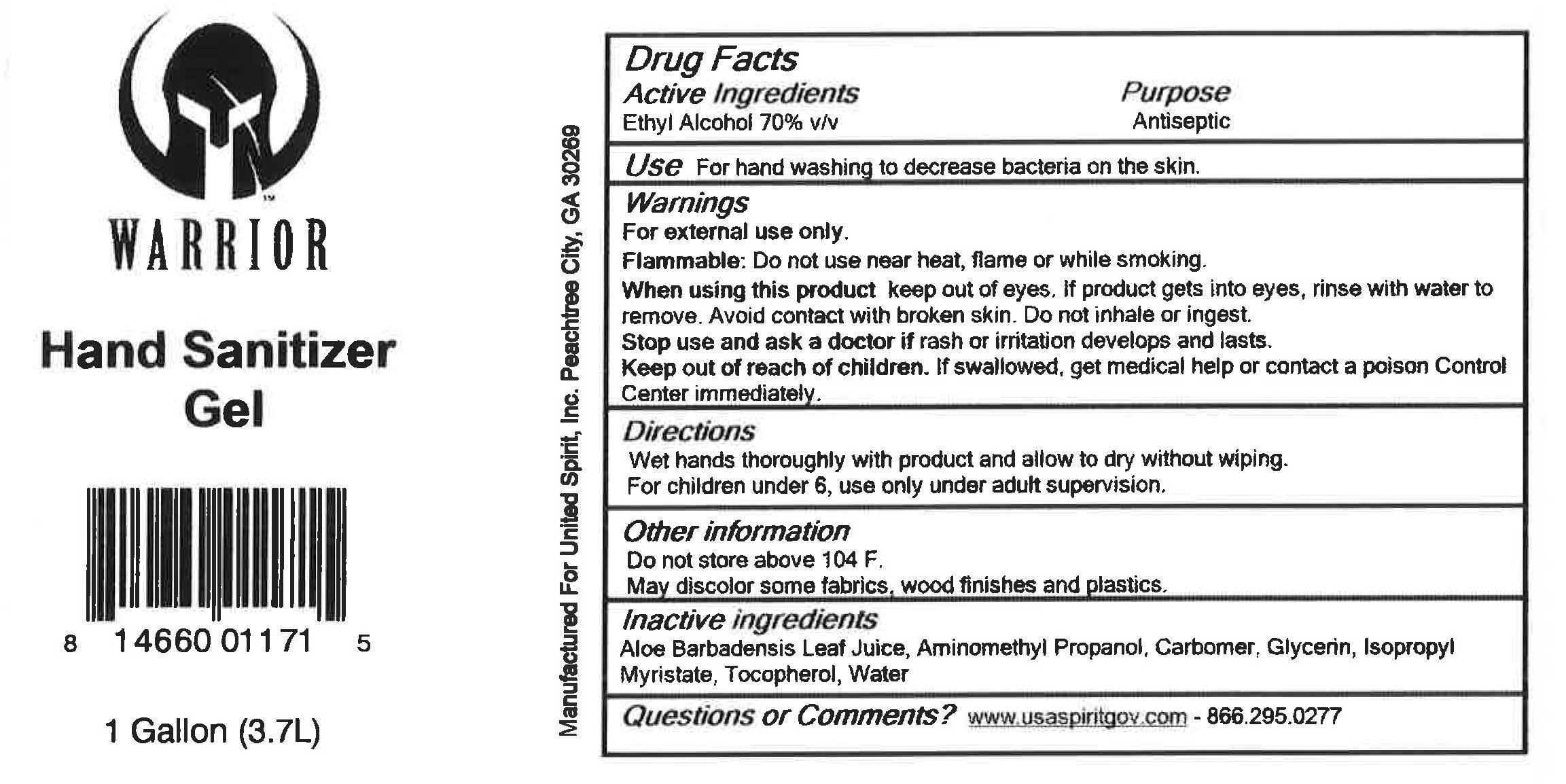 DRUG LABEL: United Spirit of America
NDC: 58443-0553 | Form: GEL
Manufacturer: Prime Enterprises
Category: otc | Type: HUMAN OTC DRUG LABEL
Date: 20220524

ACTIVE INGREDIENTS: ALCOHOL 609 mg/1 mL
INACTIVE INGREDIENTS: GLYCERIN; ISOPROPYL MYRISTATE; ALOE VERA LEAF; AMINOMETHYLPROPANOL; CARBOMER INTERPOLYMER TYPE A (ALLYL SUCROSE CROSSLINKED); TOCOPHEROL; WATER

Warrior Hand Sanitizer Gel

Active Ingredient

Ethyl Alcohol 70% v/v

Purpose

Antiseptic

Use

For hand washing to decrease bacteria on the skin.

Warnings

For external use only.

DO NOT USE

Flammable: Do not use near hear, flame or while smoking.

When using this product: Keep put of eyes. If product gets into eyes, rinse with water to remove. Avoid contact with broken skin. Do not inhale or ingest.

Stop use and ask a doctor if rash or irritation develops and lasts.

Keep out of reach of children. If swallowed, get medical help or contact a Poison Control Center immediately.

Directions

- Wet hands thoroughly with product and allow to dry without wiping.
- For children under 6, use only under adult supervision.

Other Information

- Do not store above 104°F.
- May discolor some fabrics, wood finishes and plastics.

Inactive ingredients

Aloe Barbadensis Leaf Juice, Aminomethyl Propanol, Carbomer, Glycerin, Isopropyl Myristate, Tocopherol, Water

Questions and comments

www.usaspiritgov.com - 866.295.0277